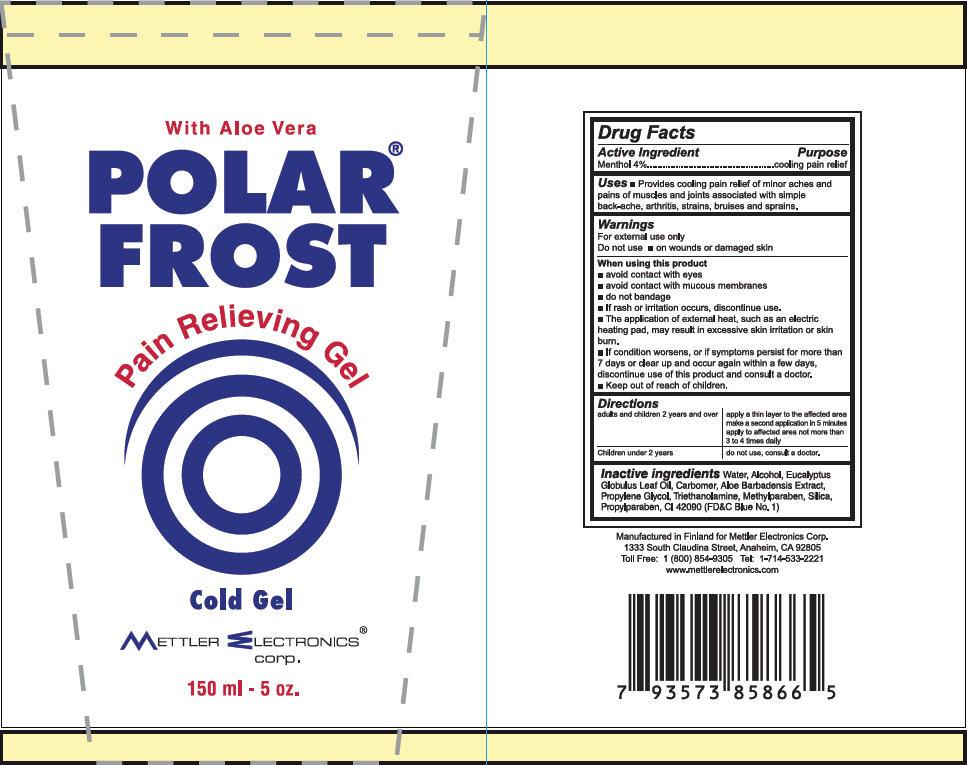 DRUG LABEL: Polar Frost Cold
NDC: 67138-533 | Form: GEL
Manufacturer: Mettler Electronics Corp.
Category: otc | Type: HUMAN OTC DRUG LABEL
Date: 20140516

ACTIVE INGREDIENTS: Menthol 40 mg/1 mL
INACTIVE INGREDIENTS: Water; Alcohol; Eucalyptus Oil; Propylene Glycol; Aloe Vera Leaf; Silicon Dioxide; Trolamine; Methylparaben; Propylparaben; Carbomer Homopolymer Type C (Allyl Pentaerythritol Crosslinked)

Polar® Frost Cold Gel

Drug Facts

Active Ingredient

Menthol 4%

Purpose

cooling pain relief

Uses

Provides cooling pain relief of minor aches and pains of muscles and joints associated with simple back-ache, arthritis, strains, bruises and sprains.

Warnings

For external use only

Do not use on wounds or damaged skin

When using this product

- avoid contact with eyes
- avoid contact with mucous membranes
- do not bandage

- If rash or irritation occurs, discontinue use.
- The application of external heat, such as an electric heating pad, may result in excessive skin irritation or skin burn.
- If condition worsens, or if symptoms persist for more than 7 days or clear up and occur again within a few days, discontinue use of this product and consult a doctor.

- Keep out of reach of children.

Directions

- Adults and children 2 years of age and older:
- Apply a thin layer to the affected area.
- Make a second application in 5 minutes.
- Apply to affected area not more than 3 to 4 times daily.
- Children under 2 years of age: Do not use, consult a doctor.

Inactive Ingredients

Water, Alcohol, Eucalyptus Globulus Leaf Oil, Carbomer, Aloe Barbadensis Extract, Propylene Glycol, Triethanolamine, Methylparaben, Silica, Propylparaben, Cl 42090 (FD&C Blue No. 1)

PRINCIPAL DISPLAY PANEL - 150 ml Tube Label

With Aloe Vera

POLAR®
FROST

Pain Relieving Gel

Cold Gel

METTLER ELECTRONICS®
corp.

150 ml - 5 oz.